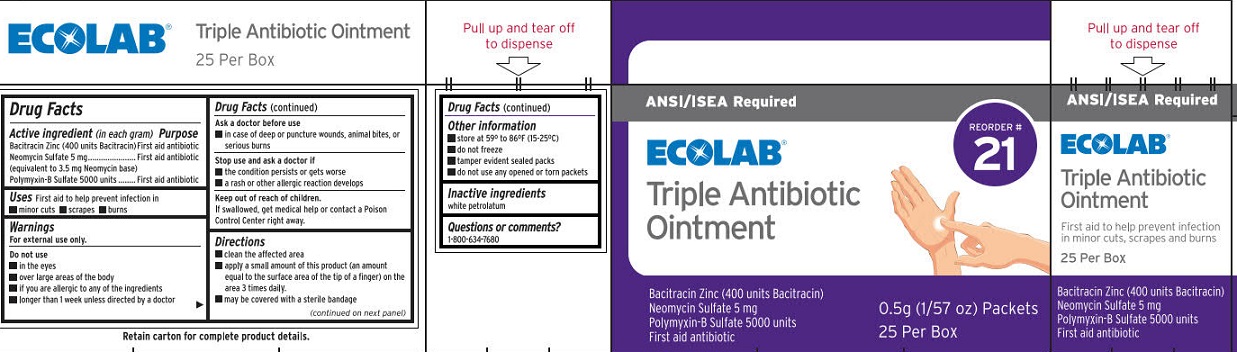 DRUG LABEL: Ecolab Triple Antibiotic
NDC: 71338-121 | Form: OINTMENT
Manufacturer: Ecolabs Food Safety Specialties, Inc.
Category: otc | Type: HUMAN OTC DRUG LABEL
Date: 20250909

ACTIVE INGREDIENTS: NEOMYCIN SULFATE 3.5 mg/1 g; POLYMYXIN B SULFATE 5000 [USP'U]/1 g; BACITRACIN ZINC 400 [USP'U]/1 g
INACTIVE INGREDIENTS: PETROLATUM

Ecolab Triple Antibiotic Ointment

Drug Facts

Active ingredient (in each gram)

Bacitracin Zinc (400 units Bacitracin)

Neomycin Sulfate (equivalent to 3.5 mg Neomyxin base)

Polymyxin -B Sulfate 5000 units

Purpose

First aid antibiotics

Uses

First aid to help prevent infection in

- minor cuts
- scrapes
- burns

Warnings

For external use only

Do not use

- in eyes
- over large areas of the body
- if you are allergic to any of the ingredients
- longer than 1 week unless directed by a doctor

Ask a doctor befor use

- in case of deep puncture wounds, animal bites, or serioius burns

Stop use and ask a doctor if

- the condition persists or gets worse
- a rash or allergic reaction develops

Keep out of reach of children.

If swallowed, get medical help and call a Poison Control Center right away.

Directions

- clean the affected area
- apply a small amount of this product (an amount equal to the surface area of the tip of your finger) on the area 3 times daily
- may be covered with a sterlle bandage

Other information

- store at 59-86°F (15-25°C)
- do not freeze
- tamper evident sealed packets
- do not use any open or torn packets

Inactive ingredients

whie petrolatum

Questions or comments?

1-800-634-7680

Ecolab Triple Antibiotic Ointment Label

ANSI/ISEA Required

Reorder # 21

ECOLAB®

Triple Antibiotic Ointment

First aid to help prevent infection in minor cuts, scrapes and burns

Bacitracin Zinc (400 units Bacitracin)

Neomycin Sulfate 5 mg

Polymyxin-B Sulfate 5000 units

First aid antibiotic

0.5g(1/57 oz) Packets

25 Per Box